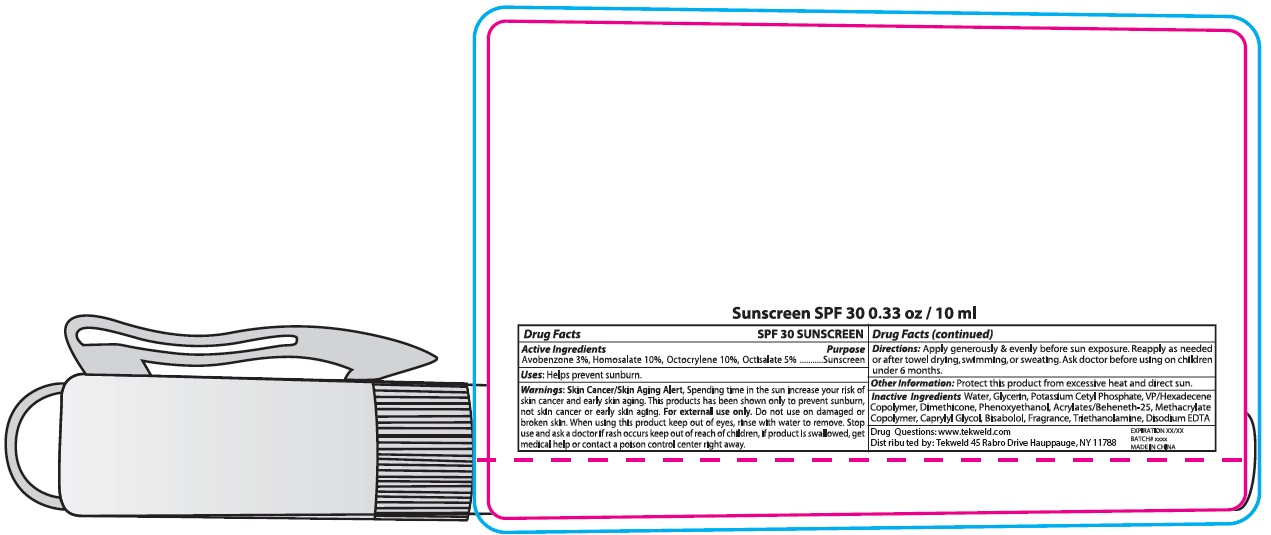 DRUG LABEL: SPF 30 Sunscreen
NDC: 71160-338 | Form: LOTION
Manufacturer: Tekweld Solutions, Inc.
Category: otc | Type: HUMAN OTC DRUG LABEL
Date: 20231227

ACTIVE INGREDIENTS: AVOBENZONE 30 mg/1 mL; HOMOSALATE 100 mg/1 mL; OCTOCRYLENE 100 mg/1 mL; OCTISALATE 50 mg/1 mL
INACTIVE INGREDIENTS: WATER; GLYCERIN; POTASSIUM CETYL PHOSPHATE; VINYLPYRROLIDONE/HEXADECENE COPOLYMER; DIMETHICONE; PHENOXYETHANOL; CAPRYLYL GLYCOL; LEVOMENOL; TROLAMINE; EDETATE DISODIUM ANHYDROUS

SPF 30 Sunscreen

Active ingredients

Avobenzone 3%,

Homosalate 10%,

Octocrylene 10%,

Octisalate 5%

Purpose

Sunscreen

Uses:

Helps prevent sunburn.

Warnings:

Skin Cancer/Skin Aging Alert,Spending time in the sun increase your risk of skin cancer and early aging. This products has been shown only to prevent sunburn, not skin cancer or early skin aging. For external use only.

Do not use

on damaged or broken skin.

When using this product

keep out of eyes, rinse with water to remove.

Stop use and ask a doctor

if rash occurs

keep out of reach of children,

if product is swallowed, get medical help or contact a poison control center right away.

Directions:

Apply generously & evenly before sun exposure. Reapply as needed or after towel drying, swimming, or sweating.Ask doctor before using on children under 6 months.

Other information:

Protect this product from excessive heat and direct sun.

Inactive Ingredients

Water, Glycerin, Potassium Cetyl Phosphate, VP/Hexadecene Copolymer, Dimethicone, Phenoxyethanol, Acrylates/Beheneth-25, Methacrylate Copolymer, Caprylyl Glycol, Bisabolol, Fragrance, Triethanolamine, Disodium EDTA

Drug Questions:

www.tekweld.com